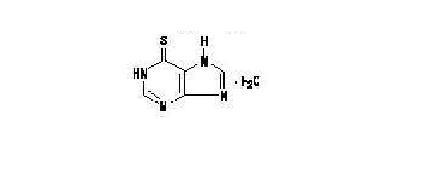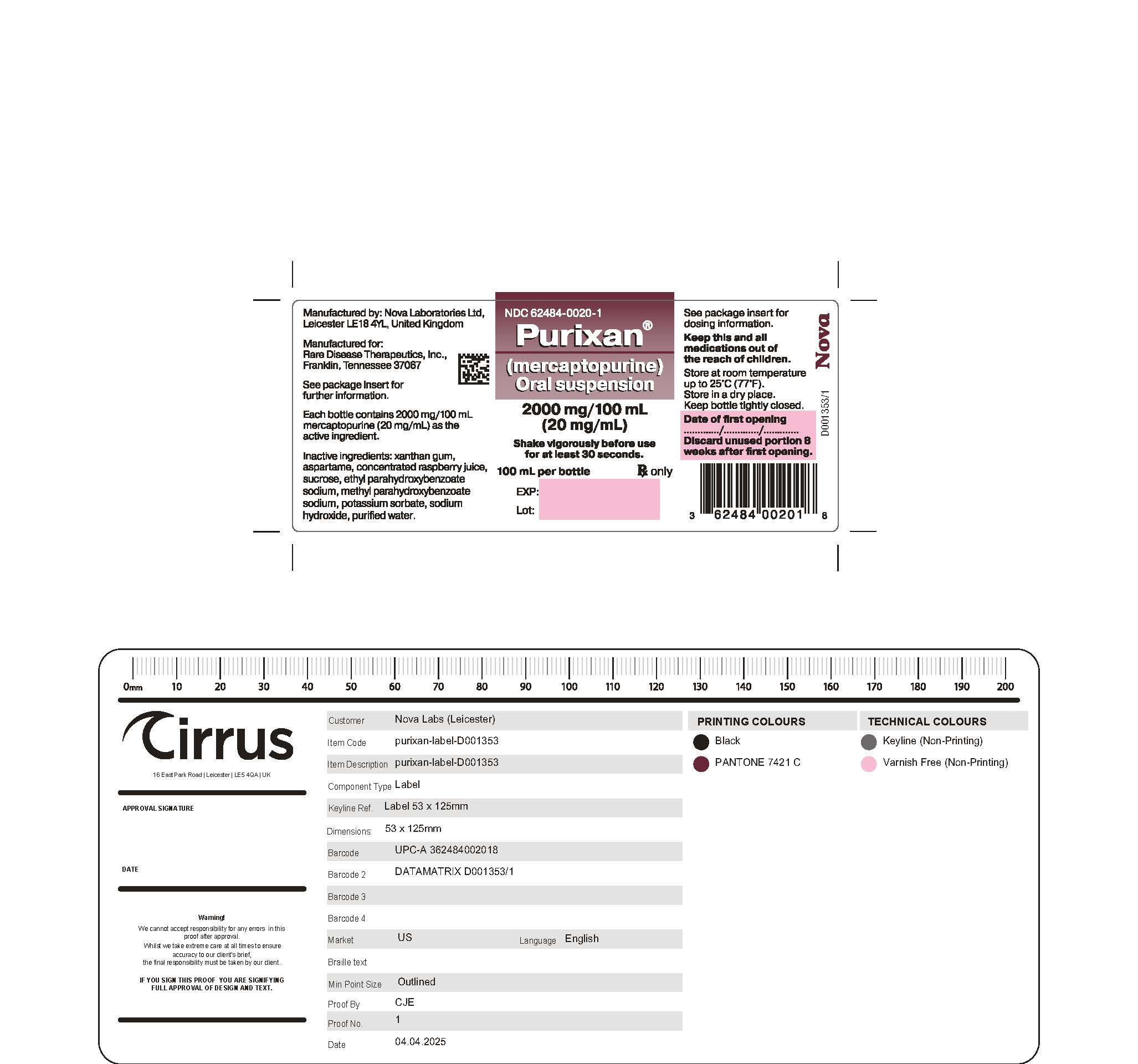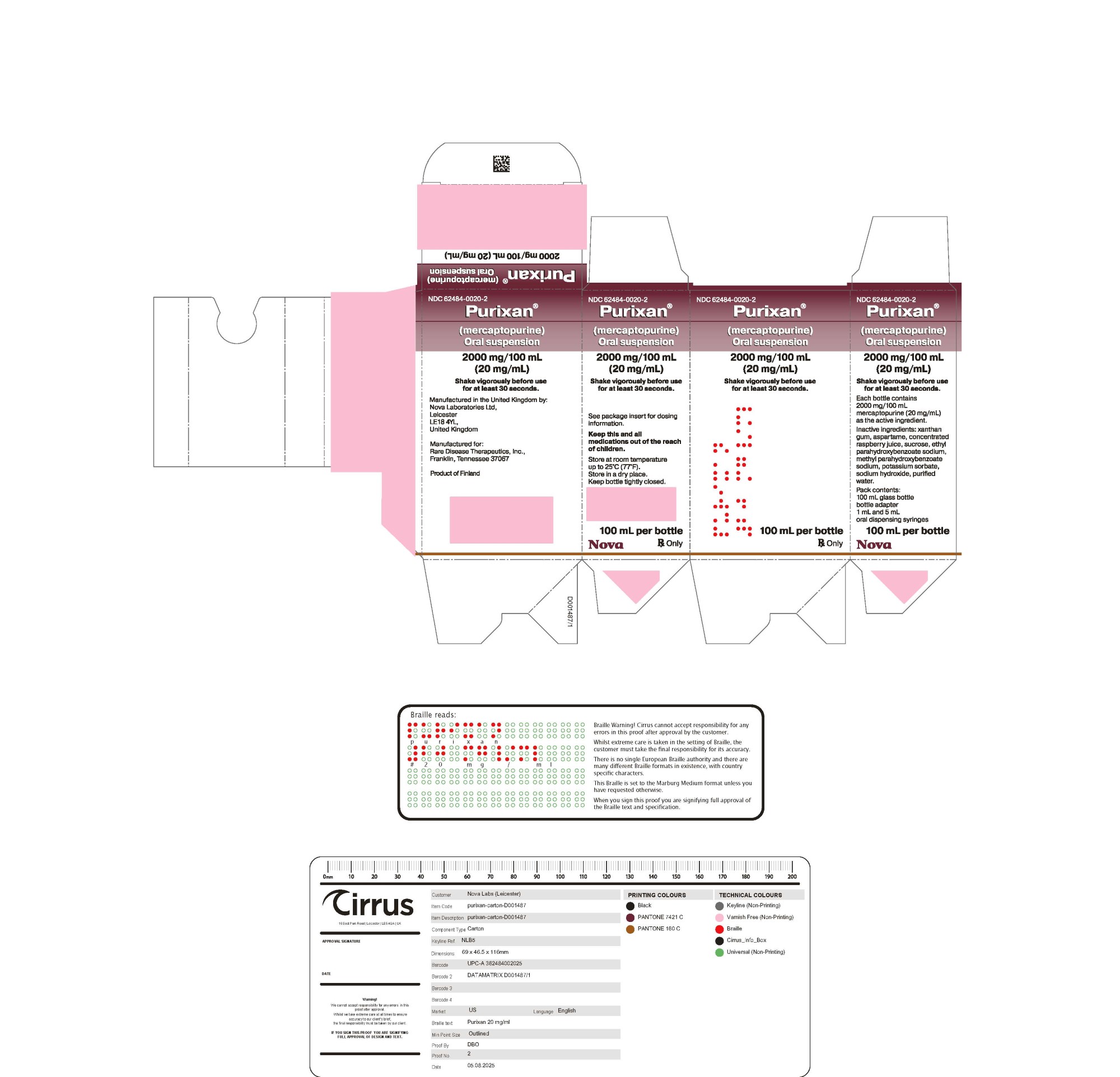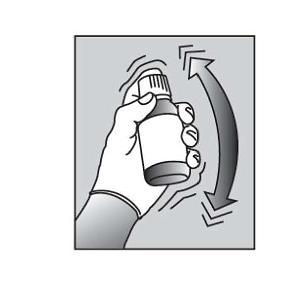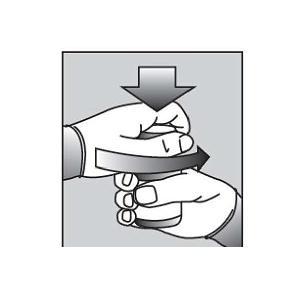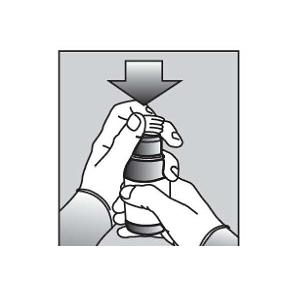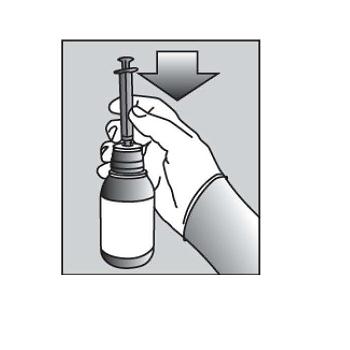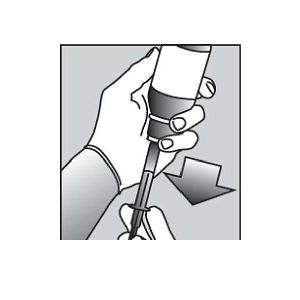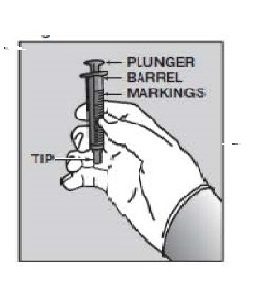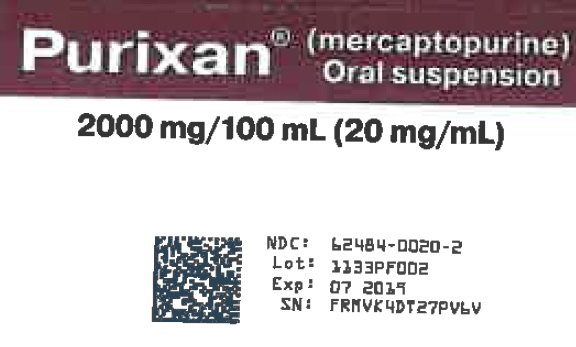 DRUG LABEL: PURIXAN
NDC: 62484-0020 | Form: SUSPENSION
Manufacturer: Nova Laboratories, Ltd
Category: prescription | Type: HUMAN PRESCRIPTION DRUG LABEL
Date: 20250820

ACTIVE INGREDIENTS: Mercaptopurine 20 mg/1 mL

HIGHLIGHTS OF PRESCRIBING INFORMATION

These highlights do not include all the information needed to use PURIXAN safely and effectively. See full prescribing information for PURIXAN.
PURIXAN(R) (mercaptopurine) oral suspension
Initial U.S. Approval: 1953

RECENT MAJOR CHANGES

Warnings and Precautions, Hepatotoxicity (5.2) | 7/2024

1 INDICATIONS AND USAGE

PURIXAN is a nucleoside metabolic inhibitor indicated for the treatment of patients with acute lymphoblastic leukemia (ALL) as part of a combination chemotherapy maintenance regimen.(1.1)

2 DOSAGE AND ADMINISTRATION

- The recommended starting dosage of PURIXAN is 1.5 mg/kg to 2.5 mg/kg (50 mg/m^2 to 75 mg/m^2) orally once daily as part of a combination chemotherapy maintenance regimen. Adjust dose to maintain desirable absolute neutrophil count and for excessive myelosuppression.(2.1)
- Renal Impairment: Use the lowest recommended starting dose or increase the dosing interval. (2.3,8.6)
- Hepatic Impairment: Use the lowest recommended starting dose. (2.3,8.7)

3 DOSAGE FORMS AND STRENGTHS

Oral suspension: 2,000 mg/100 mL (20 mg/mL). (3)

4 CONTRAINDICATIONS

- None

5 WARNINGS AND PRECAUTIONS

- Myelosuppression: Monitor complete blood count (CBC) and adjust the dose of PURIXAN for excessive myelosuppression. Consider testing in patients with severe myelosuppression or repeated episodes of myelosuppression for thiopurine S-methyltransferase (TPMT) or nucleotide diphosphatase (NUDT15) deficiency. Patients with homozygous-TPMT or homozygous-NUDT15 deficiency may require a dose reduction. (2.2,5.1)
- Hepatotoxicity: Monitor transaminases, alkaline phosphatase and bilirubin. Withhold PURIXAN at onset of hepatotoxicity. (5.2)
- Immunosuppression:Response to all vaccines may be diminished and there is a risk of infection with live virus vaccines. Consult immunization guidelines for immunocompromised pediatrics. (5.3)
- Treatment Related Malignancies: Aggressive and fatal cases of hepatosplenic T-cell lymphoma have occurred. (5.4)
- Macrophage Activation Syndrome: Monitor for and treat promptly; discontinue PURIXAN. (5.5)
- Embryo-Fetal Toxicity: Can cause fetal harm. Advise patients of reproductive potential of the potential risk to a fetus and to use effective contraception. (5.6, 8.1, 8.3)

6 ADVERSE REACTIONS

The most common adverse reaction (> 20%) is myelosuppression including anemia, neutropenia, lymphopenia and thrombocytopenia. Adverse reactions occurring in 5% to 20% of patients include anorexia, nausea, vomiting, diarrhea, malaise and rash. (6.1)
To report SUSPECTED ADVERSE REACTIONS, contact Rare Disease Therapeutics, Inc., at 1-844-472-7389 or FDA at 1-800-FDA-1088 or www.fda.gov/medwatch.

7 DRUG INTERACTIONS

- Allopurinol: Reduce the dose of PURIXAN when co-administered with allopurinol. (2.4, 7.1)
- Warfarin: PURIXAN may decrease the anticoagulant effect. (7.2)

See FDA approved patient labeling and

8 USE IN SPECIFIC POPULATIONS

- Lactation: Advise not to breastfeed. (8.2)
- Infertility: Can impair fertility. (8.3)

FULL PRESCRIBING INFORMATION

1 INDICATIONS AND USAGE

1.1 Acute Lymphoblastic Leukemia

PURIXAN is indicated for the treatment of patients with acute lymphoblastic leukemia (ALL) as part of a combination chemotherapy maintenance regimen.

2 DOSAGE AND ADMINISTRATION

2.1 Recommended Dosage

The recommended starting dose of PURIXAN is 1.5 mg/kg to 2.5 mg/kg (50 mg/m^2 to 75 mg/m^2) orally once daily as part of combination chemotherapy maintenance regimen. Take PURIXAN either consistently with or without food.
After initiating PURIXAN, monitor complete blood counts (CBC) and adjust the dose to maintain absolute neutrophil count (ANC) at a desirable level and for excessive myelosuppression. Evaluate the bone marrow in patients with prolonged myelosuppression or repeated episodes of myelosuppression to assess leukemia status and marrow cellularity.
Evaluate thiopurine S-methyltransferase (TPMT) and nucleotide diphosphatase (NUDT15) status in patients with severe myelosuppression or repeated episodes of myelosuppression [see Dosage and Administration (2.2)].
If a patient misses a dose, instruct the patient to continue with the next scheduled dose.

2.2 Dosage Modifications in Patients with TPMT and/or NUDT15 Deficiency

Consider testing for TPMT and NUDT15 deficiency in patients who experience severe myelosuppression or repeated episodes of myelosuppression [see Warnings and Precautions (5.1)and Clinical Pharmacology (12.5)].
Homozygous Deficiency in either TPMT or NUDT15
Patients with homozygous deficiency of either enzyme typically require 10% or less of the recommended dosage. Reduce the recommended starting dosage of PURIXAN in patients who are known to have homozygous TPMT or NUDT15 deficiency.
Heterozygous Deficiency in TPMT and/or NUDT15
Reduce the PURIXAN dosage based on tolerability. Most patients with heterozygous TPMT or NUDT15 deficiency tolerate recommended dosage, but some require dose reduction based on adverse reactions. Patients who are heterozygous for both TPMT and NUDT15 may require more substantial dose reductions.

2.3 Dosage Modifications in Renal and Hepatic Impairment

Renal Impairment
Use the lowest recommended starting dosage for PURIXAN in patients with renal impairment (CLcr less than 50 mL/min). Adjust the dosage to maintain absolute neutrophil count (ANC) at a desirable level and for adverse reactions [see Uses in Specific Populations (8.6)].
Hepatic Impairment
Use the lowest recommended starting dosage for PURIXAN in patients with hepatic impairment. Adjust the dosage to maintain absolute neutrophil count (ANC) at a desirable level and for adverse reactions [see Uses in Specific Populations (8.7)].

2.4 Dosage Modification with Concomitant Use of Allopurinol

Reduce the dose of PURIXAN to one-third to one-quarter of the current dosage when coadministered with allopurinol [see Drug Interactions (7.1)].

2.5 Administration

Shake the bottle vigorously for at least 30 seconds to ensure the oral suspension is well mixed. PURIXAN is a pink to brown viscous oral suspension.
Provide a press-in bottle adapter and two oral dispensing syringes (one 1 mL and one 5 mL).
Train patients or caregivers on proper handling, storage, administration, disposal and clean-up of accidental spillage prior to initiation of PURIXAN and during each visit to the clinic.
Advise patients and caregivers to use PURIXAN within 8 weeks and properly discard remaining PURIXAN after 8 weeks.
Provide instructions regarding which syringe to use and how to administer the specified dose, since PURIXAN is supplied with 1 mL and 5 mL oral dispensing syringes.
Advise patients that the oral dispensing syringe is intended for multiple uses and provide the following instructions:

- Wash the oral dispensing syringe with warm ‘soapy’ water and rinse well;
- Hold the oral dispensing syringe under water and move the plunger up and down several times to make sure the inside of the oral dispensing syringe is clean;
- Ensure the oral dispensing syringe is completely dry before use of the oral dispensing syringe again; and
- Store the oral dispensing syringe in a hygienic place with PURIXAN.

PURIXAN is a hazardous drug. Follow special handling and disposal procedures.^1

3 DOSAGE FORMS AND STRENGTHS

Oral Suspension: 2,000 mg/100 mL (20 mg/mL) pink to brown in color.

4 CONTRAINDICATIONS

None.

5.1 Myelosuppression

The most consistent, dose-related adverse reaction of PURIXAN is myelosuppression, manifested by anemia, leukopenia, thrombocytopenia, or any combination of these. Monitor CBC and adjust the dosage of PURIXAN for excessive myelosuppression [see Dosage and Administration (2.1)].
Consider testing for thiopurine S-methyltransferase (TPMT) or nucleotide diphosphatase (NUDT15) deficiency in patients with severe myelosuppression or repeated episodes of myelosuppression. TPMT genotyping or phenotyping (red blood cell TPMT activity) and NUDT15 genotyping can identify patients who have reduced activity of these enzymes. Patients with homozygous TPMT or NUDT15 deficiency may require a dose reduction, [see Dosage and Administration (2.2), Clinical Pharmacology (12.5)].
Myelosuppression can be exacerbated by coadministration with allopurinol, aminosalicylates or other products that cause myelosuppression. [see Drug Interactions (7.1, 7.3 and 7.4)]. Reduce the dosage of PURIXAN when coadministered with allopurinol [see Dosage and Administration (2.4)].

5.2 Hepatotoxicity

Mercaptopurine is hepatotoxic. There are reports of deaths attributed to hepatic necrosis associated with the administration of mercaptopurine. Hepatic injury can occur with any dosage but seems to occur with greater frequency when the recommended dosage is exceeded. In some patients, jaundice has cleared following withdrawal of mercaptopurine and reappeared with rechallenge.

Usually, clinically detectable jaundice appears early in the course of treatment (1 to 2 months); however, jaundice has been reported as early as 1 week and as late as 8 years after starting mercaptopurine. The hepatotoxicity has been associated in some cases with anorexia, diarrhea, jaundice, ascites and pruritus. Hepatic encephalopathy has occurred.

Monitor serum transaminase levels, alkaline phosphatase, and bilirubin levels at weekly intervals when first beginning therapy and at monthly intervals thereafter. Monitor liver tests more frequently in patients who are receiving PURIXAN with other hepatotoxic drugs [see Drug Interactions (7.5)] or with known pre-existing liver disease. Withhold PURIXAN at onset of hepatotoxicity.

Intrahepatic Cholestasis of Pregnancy
Postmarketing cases of intrahepatic cholestasis of pregnancy (ICP) have been reported in patients with inflammatory bowel disease who received mercaptopurine during pregnancy. PURIXAN is not indicated for use in inflammatory bowel disease [see Indications and Usage (1.1)].
Discontinue PURIXAN if ICP develops in a pregnant woman.

5.3 Immunosuppression

Mercaptopurine is immunosuppressive and may impair the immune response to infectious agents or vaccines. Due to the immunosuppression associated with maintenance chemotherapy for ALL, response to all vaccines may be diminished and there is a risk of infection with live virus vaccines. Consult immunization guidelines for immunocompromised patients.

5.4 Treatment Related Malignancies

Hepatosplenic T-cell lymphoma has been reported in patients treated with mercaptopurine for inflammatory bowel disease (IBD), an unapproved use. Mercaptopurine is mutagenic in animals and humans, carcinogenic in animals, and may increase the risk of secondary malignancies.
Patients receiving immunosuppressive therapy, including mercaptopurine, are at an increased risk of developing lymphoproliferative disorders and other malignancies, notably skin cancers (melanoma and non-melanoma), sarcomas (Kaposi's and non-Kaposi's) and uterine cervical cancer in situ. The increased risk appears to be related to the degree and duration of immunosuppression. It has been reported that discontinuation of immunosuppression may provide partial regression of the lymphoproliferative disorder.
A treatment regimen containing multiple immunosuppressants (including thiopurines) should therefore be used with caution as this could lead to lymphoproliferative disorders, some with reported fatalities. A combination of multiple immunosuppressants, given concomitantly increases the risk of Epstein-Barr virus (EBV)-associated lymphoproliferative disorders.

5.5 Macrophage Activation Syndrome

Macrophage activation syndrome (MAS) (hemophagocytic lymphohistiocytosis) is a known, life-threatening disorder that may develop in patients with autoimmune conditions, in particular with inflammatory bowel disease (IBD), and there could potentially be an increased susceptibility for developing the condition with the use of mercaptopurine (an unapproved use). If MAS occurs, or is suspected, discontinue PURIXAN. Monitor for and promptly treat infections such as EBV and cytomegalovirus (CMV), as these are known triggers for MAS.

5.6 Embryo-Fetal Toxicity

PURIXAN can cause fetal harm when administered to a pregnant woman. An increased incidence of miscarriage has been reported in women who received mercaptopurine in the first trimester of pregnancy. Adverse embryo-fetal findings, including miscarriage and stillbirth, have been reported in women who received mercaptopurine after the first trimester of pregnancy. Advise pregnant women of the potential risk to a fetus. Advise females of reproductive potential to use effective contraception during treatment with PURIXAN and for 6 months after the last dose. Advise males with female partners of reproductive potential to use effective contraception during treatment with PURIXAN and for 3 months after the last dose [see Use in Specific Populations (8.1,8.3)].

6 ADVERSE REACTIONS

The following clinically significant adverse reactions are described elsewhere in the labeling:

- Myelosuppression [see Warnings and Precautions (5.1)]
- Hepatotoxicity [see Warnings and Precautions (5.2)]
- Immunosuppression [see Warnings and Precautions (5.3)]
- Treatment Related Malignancies [see Warnings and Precautions (5.4)]
- Macrophage Activation Syndrome [see Warnings and Precautions (5.5)]

6.1 Clinical Trials Experience

Because clinical trials are conducted under widely varying conditions, adverse reaction rates observed in the clinical trials of a drug cannot be directly compared to rates in the clinical trials of another drug and may not reflect the rates observed in practice.
Based on multicenter cooperative group ALL trials, the most common adverse reaction occurring in > 20% of patients was mylelosuppression including anemia, neutropenia, lymphopenia and thrombocytopenia. Adverse reactions occurring in 5% to 20% of patients included anorexia, nausea, vomiting, diarrhea, malaise, and rash. Adverse reactions occurring in < 5 % of patients included urticaria, hyperuricemia, oral lesions, elevated transaminases, hyperbilirubinemia, hyperpigmentation, infections, and pancreatitis. Oral lesions resemble thrush rather than antifolic ulcerations. Delayed or late toxicities include hepatic fibrosis, hyperbilirubinemia, alopecia, pulmonary fibrosis, oligospermia and secondary malignancies. [see Warnings and Precautions (5.1, 5.2)].
Drug fever has been reported with PURIXAN.

6.2 Postmarketing Experience

The following adverse reactions have been identified during postapproval use of PURIXAN. Because these reactions are reported voluntarily from a population of uncertain size, it is not always possible to reliably estimate their frequency or establish a causal relationship to drug exposure. These reactions include: photosensitivity, hypoglycemia, portal hypertension, intrahepatic cholestasis of pregnancy (ICP), pellagra, and erythema nodosum.

7.1 Allopurinol

Allopurinol can inhibit the first-pass oxidative metabolism of mercaptopurine by xanthine oxidase, which can lead to an increased risk of mercaptopurine adverse reactions [see Warnings and Precautions (5.1), Adverse Reactions (6.1)]. Reduce the dose of PURIXAN when coadministered with allopurinol [see Dosage and Administration (2.4)].

7.2 Warfarin

The coadministration of PURIXAN with warfarin may decrease the anticoagulant effectiveness of warfarin. Monitor the international normalized ratio (INR) in patients receiving warfarin and adjust the warfarin dosage as appropriate.

7.3 Myelosuppressive Products

PURIXAN can cause myelosuppression. Myelosuppression may be increased when PURIXAN is coadministered with other drugs that cause myelosuppression. Enhanced myelosuppression has been noted in some patients receiving trimethoprim-sulfamethoxazole. Monitor the CBC and adjust the dose of PURIXAN for excessive myelosuppression [see Dosage and Administration (2.1), Warnings and Precautions (5.1)].

7.4 Aminosalicylates

Aminosalicylates (e.g., mesalamine, olsalazine or sulfasalazine) may inhibit the TPMT enzyme, which may increase the risk of myelosuppression when coadministered with PURIXAN. When aminosalicylates and PURIXAN are coadministered, use the lowest possible doses for each drug and monitor more frequently for myelosuppression [see Warnings and Precautions (5.1)].

7.5 Hepatotoxic Products

PURIXAN can cause hepatotoxicity. Hepatotoxicity may be increased when PURIXAN is coadministered with other products that cause hepatotoxicity. Monitor liver tests more frequently in patients who are receiving PURIXAN with other hepatotoxic products [see Warnings and Precautions (5.2)].

7.6 Methotrexate

PURIXAN dosage may need adjustment when administered concomitantly with high dose methotrexate [see Warnings and Precautions (5.1)]. Mercaptopurine exposure increases with concomitant methotrexate use [see Clinical Pharmacology (12.3)] which may increase the risk of PURIXAN adverse reactions. The mechanism of this interaction has not been fully characterized [see Clinical Pharmacology (12.3)].

8.1 Pregnancy

Risk Summary
PURIXAN can cause fetal harm when administered to a pregnant woman [see Clinical Pharmacology (12.1)]. Pregnant women who receive mercaptopurine have an increased incidence of miscarriage and stillbirth (see Data). Advise pregnant women of the potential risk to a fetus.
The estimated background risk of major birth defects and miscarriage for the indicated population(s) is unknown. All pregnancies have a background risk of birth defect, loss, or other adverse outcomes. In the U.S. general population, the estimated background risk of major birth defects and miscarriage in clinically recognized pregnancies is 2% to 4% and 15% to 20%, respectively.
Data
Human Data
Women receiving mercaptopurine in the first trimester of pregnancy have an increased incidence of miscarriage; the risk of malformation in offspring surviving first trimester exposure is not known. In a series of 28 women receiving mercaptopurine after the first trimester of pregnancy, 3 mothers died prior to delivery, 1 delivered a stillborn child, and 1 aborted; there were no cases of macroscopically abnormal fetuses.
Animal Data
Mercaptopurine was embryo-lethal and teratogenic in several animal species (rat, mouse, rabbit, and hamster) at doses less than the recommended human dose.

8.2 Lactation

Risk Summary
There are no data on the presence of mercaptopurine or its metabolites in human milk, the effects on the breastfed child or the effects on milk production. Because of the potential for serious adverse reactions in the breastfed child, advise women not to breastfeed during treatment with PURIXAN and for 1 week after the last dose.

8.3 Females and Males of Reproductive Potential

PURIXAN can cause fetal harm when administered to pregnant women [see Use in Specific Populations (8.1)].
Pregnancy Testing
Verify the pregnancy status in females of reproductive potential prior to initiating PURIXAN [see Use in Specific Populations (8.1)].
Contraception
Females
Advise females of reproductive potential to use effective contraception during treatment with PURIXAN and for 6 months after the last dose.
Males
Based on genotoxicity findings, advise males with female partners of reproductive potential to use effective contraception during treatment with PURIXAN and for 3 months after the last dose [see Nonclinical Toxicology (13.1)].
Infertility
Females and Males
Based on findings from animal studies, PURIXAN can impair female and male fertility [see Nonclinical Toxicology (13.1)]. The long-term effects of mercaptopurine on female and male fertility, including the reversibility have not been studied.

8.4 Pediatric Use

Safety and effectiveness of PURIXAN has been established in pediatric patients. Use of PURIXAN in pediatrics is supported by evidence from the published literature and clinical experience. Symptomatic hypoglycemia has been reported in pediatric patients with ALL receiving mercaptopurine. Reported cases were in pediatrics less than 6 years or with a low body mass index.

8.5 Geriatric Use

Clinical studies of mercaptopurine did not include sufficient numbers of subjects aged 65 and over to determine whether they respond differently from younger subjects. Other reported clinical experience has not identified differences in responses between the elderly and younger patients. In general, dose selection for an elderly patient should be cautious, usually starting at the low end of the dosing range, reflecting the greater frequency of decreased hepatic, renal, or cardiac function, and of concomitant disease or another drug therapy.

8.6 Renal Impairment

Use the lowest recommended starting dosage for PURIXAN or increase the dosing interval to every 36 to 48 hours in patients with renal impairment (CLcr less than 50 mL/min). Adjust the dose to maintain absolute neutrophil count (ANC) at a desirable level and for adverse reactions [see Dosage and Administration (2.3)].

8.7 Hepatic Impairment

Use the lowest recommended starting dosage for PURIXAN in patients with hepatic impairment. Adjust the dose to maintain absolute neutrophil count (ANC) at a desirable level and for adverse reactions [see Dosage and Administration (2.3)].

10 OVERDOSAGE

Signs and symptoms of mercaptopurine overdosage may be immediate (anorexia, nausea, vomiting, and diarrhea) or delayed (myelosuppression, liver dysfunction, and gastroenteritis). Dialysis cannot be expected to clear mercaptopurine. Hemodialysis is thought to be of marginal use due to the rapid intracellular incorporation of mercaptopurine into active metabolites with long persistence.
Withhold PURIXAN immediately if severe or life-threatening adverse reactions occur during treatment. If a patient is seen immediately following an accidental overdosage, it may be useful to induce emesis.

11 DESCRIPTION

Mercaptopurine, a nucleoside metabolic inhibitor. The chemical name is 1,7-dihydro-6H-purine-6-thione monohydrate. The molecular formula is C5H4N4S•H2O and the molecular weight is 170.20. The structural formula is:

Mercaptopurine is a yellow, odorless or practically odorless, crystalline powder. It is practically insoluble in water with pKa 7.8, 11.2.
PURIXAN (mercaptopurine) oral suspension contains 2,000 mg/100 mL (20 mg/mL) of mercaptopurine. The suspension also contains the following inactive ingredients: xanthan gum, aspartame, concentrated raspberry juice, sucrose, ethyl parahydroxybenzoate sodium, methyl parahydroxybenzoate sodium, potassium sorbate, sodium hydroxide and purified water. PURIXAN is a pink to brown viscous suspension.

12 CLINICAL PHARMACOLOGY

12.1 Mechanism of Action

Mercaptopurine is a purine analog that undergoes intracellular transport and activation to form metabolites including thioguanine nucleotides (TGNs). Incorporation of TGNs into DNA or RNA results in cell-cycle arrest and cell death. TGNs and other mercaptopurine metabolites are also inhibitors of de novo purine synthesis and purine nucleotide interconversions. Mercaptopurine was cytotoxic to proliferating cancer cells in vitro and had antitumor activity in mouse tumor models. It is not known which of the biochemical effects of mercaptopurine and its metabolites are directly or predominantly responsible for cell death.

12.2 Pharmacodynamics

Exposure-Response Relationships
Mercaptopurine exposure-response relationships and the time course of pharmacodynamics response are unknown.

12.3 Pharmacokinetics

Following a single oral dose of PURIXAN 50 mg under fasted conditions to adult healthy subjects, the median (min – max) AUC0-INF was 137 h∙ng/mL (77 – 268 h∙ng/mL) and Cmax was 93 ng/mL (40 – 204 ng/mL).
Absorption
PURIXAN is absorbed after oral administration with a median (min – max) Tmax of 0.75 (0.33 – 2.5) hours.
Effect of foods
Food has been shown to decrease the exposure of mercaptopurine.
Distribution
The volume of distribution exceeds total body water with a mean volume of distribution of approximately 0.9 L/kg. There is negligible entry of mercaptopurine into cerebrospinal fluid.
Plasma protein binding averages 19% over the concentration range 10 to 50 mcg/L.
Elimination
The median (min – max) elimination half-life (t1/2) was 1.3 (0.9 – 5.4) hours.
Metabolism
Mercaptopurine is inactivated via two major pathways. One is thiol methylation, which is catalyzed by the polymorphic enzyme thiopurine S-methyltransferase (TPMT), to form the inactive metabolite methyl-mercaptopurine. The second inactivation pathway is oxidation, which is catalyzed by xanthine oxidase. The product of oxidation is the inactive metabolite 6-thiouric acid.
Elimination
After oral administration of mercaptopurine, urine contains intact mercaptopurine, thiouric acid (formed by direct oxidation by xanthine oxidase, probably via 6-mercapto-8-hydroxypurine), and a number of 6-methylated thiopurines. In one subject, a total of 46% of the dose could be accounted for in the urine (as parent drug and metabolites) in the first 24 hours.
Specific Populations
Pediatrics Patients
Wide inter individual variations in systemic exposure is observed. Following oral administration of 50 mg/m^2 mercaptopurine in 10 children, median plasma concentrations 1 hour post dose was 0.35 (range 0.03 to 1.03) μM and median AUC1–5hours was 56 (range 23 to 65) μM·min. Tmax ranged from 1 to 3 hours.
Drug Interactions Studies
Methotrexate: Mercaptopurine AUC increased by approximately 31% when coadministered with oral methotrexate 20 mg/m^2. Mercaptopurine AUC increased by 69% when coadministered with IV methotrexate 2 g/m^2, and by 93% when coadministered with IV methotrexate 5 g/m^2.

12.5 Pharmacogenomics

Several published studies indicate that patients with reduced TPMT or NUDT15 activity receiving usual doses of mercaptopurine, accumulate excessive cellular concentrations of active 6-TGNs, and are at higher risk for severe myelosuppression [see Warnings and Precautions (5.1)]. In a study of 1028 children with ALL, the approximate tolerated mercaptopurine dosage for patients with TPMT and/or NUDT15 deficiency on mercaptopurine maintenance therapy (as a percentage of the planned dosage) was as follows: heterozygous for either TPMT or NUDT15, 50-90%; heterozygous for both TPMT and NUDT15, 30-50%; homozygous for either TPMT or NUDT15, 5-10%.
Approximately 0.3% (1:300) of patients of European or African ancestry have two loss-of-function alleles of the TPMT gene and have little or no TPMT activity (homozygous deficient or poor metabolizers), and approximately 10% of patients have one loss-of-function TPMT allele leading to intermediate TPMT activity (heterozygous deficient or intermediate metabolizers). The TPMT*2, TPMT*3A, and TPMT*3C alleles account for about 95% of individuals with reduced levels of TPMT activity.
NUDT15 deficiency is detected in <1% of patients of European or African ancestry. Among patients of East Asian ancestry (i.e., Chinese, Japanese, Vietnamese), 2% have two loss-of-function alleles of the NUDT15 gene, and approximately 21% have one loss-of-function allele. The p.R139C variant of NUDT15 (present on the *2 and *3 alleles) is the most commonly observed, but other less common loss-of-function NUDT15 alleles have been observed.
Consider all clinical information when interpreting results from phenotypic testing used to determine the level of thiopurine nucleotides or TPMT activity in erythrocytes, since some coadministered drugs can influence measurement of TPMT activity in blood, and blood from recent transfusions will misrepresent a patient’s actual TPMT activity [see Dosage and Administration (2.2) and Warnings and Precautions (5.1)].

13 NONCLINICAL TOXICOLOGY

13.1 Carcinogenesis, Mutagenesis, Impairment of Fertility

Mercaptopurine is carcinogenic in animals.
Mercaptopurine causes chromosomal aberrations in cells derived from animals and humans and induces dominant-lethal mutations in the germs cells of male mice.
Mercaptopurine can impair fertility. In mice, surviving female offspring of mothers who received chronic low doses of mercaptopurine during pregnancy were found sterile, or if they became pregnant, had smaller litters and more dead fetuses as compared to control animals.

15 REFERENCES

1. OSHA Hazardous Drugs. OSHA. http://www.osha.gov/SLTC/hazardousdrugs/index.html

16 HOW SUPPLIED/STORAGE AND HANDLING

PURIXAN (mercaptopurine) oral suspension is supply as 2,000 mg/100 mL (20 mg/mL) is a pink to brown viscous liquid in amber glass multiple-dose bottles. In addition, a press-in bottle adapter and two oral dispensing syringes (one 1 mL and one 5 mL) are provided.
Each carton NDC 62484-0020-2 contains 1 bottle of PURIXAN NDC 62484-0020-1.

- Store PURIXAN between 59ºF to 77ºF (15ºC to 25ºC). Store in a dry place.

PURIXAN is a hazardous drug. Follow special handling and disposal procedures.^1

17 PATIENT COUNSELING INFORMATION

Advise the patients and caregivers to read the FDA-approved patient labelling (Patient Information and Instructions for Use).
Major Adverse Events
Advice patients and caregivers that PURIXAN can cause myelosuppression, hepatotoxicity, and gastrointestinal toxicity. Advise patients to contact their healthcare provider if they experience fever, sore throat, jaundice, nausea, vomiting, signs of local infection, bleeding from any site, or symptoms suggestive of anemia [see Warnings and Precautions (5.1, 5.2, 5.3)].
Proper Preparation and Administration
Advise patients or caregivers on proper handling, storage, preparation, administration, and disposal and clean-up of accidental spillage of the medication prior to initiation and on each visit to the clinic [see Dosage and Administration (2.5)].
Embryo-Fetal Toxicity

- Advise pregnant women of the potential risk to a fetus. Advise females of reproductive potential to inform their healthcare provider of a known or suspected pregnancy [see Warnings and Precautions (5.2, 5.6), Use in Specific Populations (8.1)].
- Advise females of reproductive potential to use effective contraception during treatment with PURIXAN and for 6 months after the last dose [see Use in Specific Populations (8.3)].
- Advise males with female partners of reproductive potential to use effective contraception during treatment with PURIXAN and for 3 months after the last dose [see Use in Specific Populations (8.3), Nonclinical Toxicology (13.1)].

Lactation
Advise women not to breastfeed during treatment with PURIXAN and for 1 week after the last dose [see Use in Specific Populations (8.2)].
Infertility
Advise males and females of reproductive potential that PURIXAN can impair fertility [see Use in Specific Populations (8.3)].
Other Adverse Reactions
Instruct patients to minimize sun exposure due to risk of photosensitivity [see Adverse Reactions (6.2)].

Manufactured by:
Nova Laboratories Ltd
Leicester
LE 18 4YL
United Kingdom

Manufactured for:
Rare Disease Therapeutics
2550 Meridian Blvd., Suite 150
Franklin, TN 37067
www.raretx.com

Part Number: D001355/1

PATIENT INFORMATION
PURIXAN®(pure-ee-zan)
(mercaptopurine)
oral suspension

What is PURIXAN?
PURIXAN is a prescription medicine used along with other medicines to treat people with acute lymphoblastic leukemia (ALL).

What should I tell my healthcare provider before taking PURIXAN?
Before you take PURIXAN, tell your healthcare provider about all of your medical conditions,including if you:

• have kidney or liver problems.
• have a condition where your body produces too little of the enzyme thiopurine methyltransferase (TPMT) or the enzyme nucleotide diphosphatase (NUDT15).
• have recently received or plan to receive a vaccine.
• are pregnant or plan to become pregnant. PURIXAN can harm your unborn baby.
If you are a female who is able to become pregnant:

o Your healthcare provider will do a pregnancy test before you start treatment with PURIXAN.
o Use an effective method of birth control (contraception) during treatment with PURIXAN and for 6 months after your last dose. Talk with your healthcare provider about birth control methods you can
use during this time.
o Tell your healthcare provider right away if you become pregnant or think you are pregnant during treatment with PURIXAN.

If you are a male with a female partner who is able to become pregnant:

o Use effective birth control (contraception) during treatment with PURIXAN and for 3 months after your last dose.
o Tell your healthcare provider right away if your female partner becomes pregnant or thinks she is pregnant during your treatment with PURIXAN.

- are breastfeeding or plan to breastfeed. Do not breastfeed during treatment with PURIXAN and for at least 1 week after your last dose.
- Tell your healthcare provider about all the medicines you take,including prescription and over-the-counter medicines, vitamins, and herbal supplements.

How should I take PURIXAN?

- See the detailed “Instructions for Use” that comes with PURIXAN for information about the right way to measure and take a dose of PURIXAN.
- Take PURIXAN exactly as your healthcare provider tells you. Do not stop taking PURIXAN or change your dose without talking to your healthcare provider.
- Take PURIXAN by mouth 1 time each day.
- If PURIXAN comes into contact with skin, eyes, or clothes?
  • Remove contaminated clothing.
  • Wash skin or eyes immediately with water.
  • Contact with skin or eyes can cause hypersensitive reactions resulting in rash, redness, itching and inflammation. If symptoms appear seek medical attention.
- During treatment with PURIXAN, your healthcare provider will do blood tests regularly to check your blood cell counts and liver function. Your healthcare provider may change your dose if you have side effects.
- If you miss a dose of PURIXAN, call your healthcare provider for advice.
- If you take too much PURIXAN, call your healthcare provider or go to the nearest emergency room right away.

What should I avoid while taking PURIXAN?
PURIXAN can make your skin more sensitive to sunlight. Protect yourself from sunlight during treatment with PURIXAN.

What are the possible side effects of PURIXAN?
PURIXAN can cause serious side effects, including:

- Decreased blood cell countsare common with PURIXAN, but can also be severe. PURIXAN affects your bone marrow and can cause decreased white blood cells, red blood cells, and platelets. Decreased blood cell counts can make you more likely to develop infections, bleeding, or anemia. If you take certain medicines during treatment with PURIXAN, it could make the effects on your bone marrow worse. Tell your healthcare provider if you develop any of the following symptoms during treatment with PURIXAN:
  • fever
  • sore throat
  • cuts or wounds that are red, or swollen, or are draining
  • any bleeding
  • tiredness or weakness
  • shortness of breath
- Liver problems.Increases in liver function test results are common with PURIXAN, but you can also develop severe liver problems with PURIXAN that can lead to death. Your healthcare provider may tell you to stop taking PURIXAN if you develop liver problems. Tell your healthcare provider right away if you develop any of the following symptoms of a liver problem during treatment with PURIXAN:
  • decreased appetite
  • diarrhea
  • nausea or vomiting
  • yellowing of your skin or the whites of your eyes
  • a build-up of fluid in your stomach-area (ascites)

• Possible increased risk of other cancers.Talk with your healthcare provider about your risk of other cancers if you take PURIXAN.
Less common side effects of PURIXAN include:loss of appetite, nausea, vomiting, diarrhea, generally do not feel well and rash.
Low blood sugar (hypoglycemia) can happen, especially in children under six years of age.
Tell your healthcare provider if you have any side effect that bothers you or that does not go away. These are not all the possible side effects of PURIXAN.
Call your doctor for medical advice about side effects. You may report side effects to FDA at 1-800-FDA-1088.

How should I store PURIXAN?

- PURIXAN comes in a bottle with a child-resistant cap.
- Store PURIXAN between 59ºF to 77ºF (15ºC to 25ºC), in a dry place. Do not store above 25°C.
- Store the oral dispensing syringe in a clean place, with the medicine.
- PURIXAN oral suspension should be used within 8 weeks after opening the bottle. Dispose of (throw away) any unused medicine after 8 weeks.
- Do not use after the expiry date which is stated on the carton and the bottle after ‘EXP’.
- Keep the bottle tightly closed to prevent spoilage of the medicine and reduce the risk of accidental spillage.
- Keep PURIXAN out of the reach of children, preferably in a locked cupboard. If a child accidentally takes PURIXAN, it could cause death.

How should I dispose of PURIXAN?

- This medicine should not be disposed of in wastewater or household waste. Ask your pharmacist how to dispose of (throw away) PURIXAN that is no longer needed.

General information about the safe and effective use of PURIXAN.
Medicines are sometimes prescribed for purposes other than those listed in a Patient Information leaflet. Do not use PURIXAN for a condition for which it was not prescribed. Do not give PURIXAN to other people, even if they have the same symptoms you have. It could harm them. You can ask your healthcare provider or pharmacist for information about PURIXAN that is written for health professionals.

What are the ingredients in PURIXAN?
Active ingredient: mercaptopurine
Inactive ingredients: xanthan gum, aspartame, concentrated raspberry juice, sucrose, ethyl parahydroxybenzoate sodium, methyl parahydroxybenzoate sodium, potassium sorbate, sodium hydroxide and purified water.
Manufactured by: Nova Laboratories Ltd, Leicester, LE18 4YL, United Kingdom
Manufactured for: Rare Disease Therapeutics, Inc., 2550 Meridian Blvd. Suite 150, Franklin, TN 37067
For more information, go to www.purixan-us.com.
Part Number: D001354/1

This Patient information has been approved by the U.S. Food and Drug Administration
Revised: April 2020

INSTRUCTIONS FOR USE
PURIXAN® (pure-ee-zan)
mercaptopurine)
oral suspension
20 mg/mL

Read these Instructions for Use before you start taking PURIXAN, and each time you get a refill. There may be new information. This information does not take the place of talking to your healthcare provider about your medical condition or your treatment.

Important information about measuring PURIXAN oral suspension

• Always use the oral dispensing syringe provided with your PURIXAN oral suspension to make sure you measure the right amount.
• You will be provided:

- 1 bottle of PURIXAN oral suspension
- 1 bottle adapter
- 2 oral dispensing syringes (one 1 mL and one 5 mL)

If you did not receive an oral dispensing syringe with your PURIXAN oral suspension, ask your pharmacist to give you one.
You will need disposable gloves.

Important Information You Need to Know Before Administering PURIXAN:

1. | Wash your hands well with soap and water before and after administering a dose.
2. | Put on disposable gloves before handling PURIXAN.
3. | Shake the bottle vigorously for at least 30 seconds to make sure that the medicine is well mixed (See Figure A). | Figure A
4. | Remove the child-resistant bottle cap (See Figure B). | Figure B
5. | Push the ribbed end of the bottle adapter into the neck of the bottle until it is firmly in place. The bottom edge of the adapter should fully contact the top rim of the bottle (See Figure C). Do not remove the adapter from the bottle after it is inserted. | Figure C
Preparing a dose of PURIXAN:
6. | Hold the bottle upright. Remove the bottle cap by turning in the direction of the arrow (See Figure B).
7. | Push the tip of the oral dispensing syringe into the hole in the bottle adapter (See Figure D and Figure E). | Figure DFigure E
8. | Turn the bottle upside down (See Figure F). | Figure F
9. | Pull back slowly on the plunger of the oral dispensing syringe to withdraw the prescribed dose of PURIXAN. Pull the plunger back to the mL mark of the syringe that corresponds to the dose prescribed (Figure F). If you are not sure about how much medicine to draw into the oral dispensing syringe, always ask your doctor, pharmacist or nurse for advice.
10. | Leave the oral dispensing syringe in the bottle adapter and turn the bottle right-side up. Place the bottle onto a flat surface. Hold the oral dispensing syringe by the barrel and carefully remove it from the adapter. Do not hold the oral dispensing syringe by the plunger, because the plunger may come out.
11. | Place the tip of the oral dispensing syringe in your mouth and aim the tip toward the inside of your cheek.
12. | Gently squirt the PURIXAN oral suspension into your mouth by pushing on the plunger until the oral dispensing syringe is empty. Swallow the medicine.; - Do notforcefully push on the plunger. - Do notsquirt the medicine to the back of your mouth or throat. This may cause you to choke.
13. | Remove the oral dispensing syringe from your mouth.
14. | Swallow the dose of oral suspension then drink some water, making sure no medicine is left in your mouth.
15. | Put the cap back on the bottle with the adapter left in place. Close the cap tightly.
16. | Wash the oral dispensing syringe with warm soapy water and rinse well. Hold the oral dispensing syringe under water and move the plunger up and down several times to make sure the inside of the oral dispensing syringe is clean. Let the oral dispensing syringe dry completely before you use it again for dosing. Do not throw away the oral dispensing syringe after use.

Ingredients in PURIXAN

Active ingredient: mercaptopurine

Inactive ingredients: xanthan gum, aspartame, concentrated raspberry juice, sucrose, ethyl parahydroxybenzoate sodium, methyl parahydroxybenzoate sodium, potassium sorbate, sodium hydroxide and purified water.

Storing PURIXAN

- Store PURIXAN between 59ºF to 77ºF (15ºC to 25ºC), in a dry place. Do not store above 25°C.
- Store the oral dispensing syringe in a clean place, with the medicine.
- PURIXAN oral suspension should be used within 8 weeks after opening the bottle. Dispose of (throw away) any unused medicine after 8 weeks.
- Do not use after the expiry date which is stated on the carton and the bottle after ‘EXP’.
- Keep the bottle tightly closed to prevent spoilage of the medicine and reduce the risk of accidental spillage.
- Keep PURIXAN oral suspension and all medicines out of the reach of children, preferably in a locked cupboard. If a child accidentally takes PURIXAN, it could cause death.Ask your pharmacist how to dispose of (throw away) PURIXAN that is no longer needed.

Disposing of PURIXAN?

- Ask your pharmacist how to dispose of PURIXAN that is expired or no longer required. Medicines should not be disposed of via wastewater or household waste.

Clean Up Spillage of PURIXAN
Use appropriate personal protective equipment (disposable gloves and eye protection). Mop up and contain spill material in a compatible container. Wash your hands thoroughly afterwards.

PURIXAN contact with Skin, Eyes, or Clothes

- Remove and launder contaminated clothing.
- Wash skin or eyes immediately with water.

Contact with skin or eyes can cause hypersensitive reactions resulting in rash, redness, itching and inflammation. If symptoms appear, seek medical attention.

Manufactured by: Nova Laboratories Ltd, Leicester, LE18 4YL, United Kingdom
Manufactured for: Rare Disease Therapeutics, Inc., 2550 Meridian Blvd. Suite 150, Franklin, TN 37067
Part Number: D001356/1
This “Instructions for Use” has been approved by the U.S. Food and Drug Administration Revised: April 2025

PACKAGE LABEL

Purixan Carton label

Serialization Example of Purixan Carton label

Purixan Bottle label